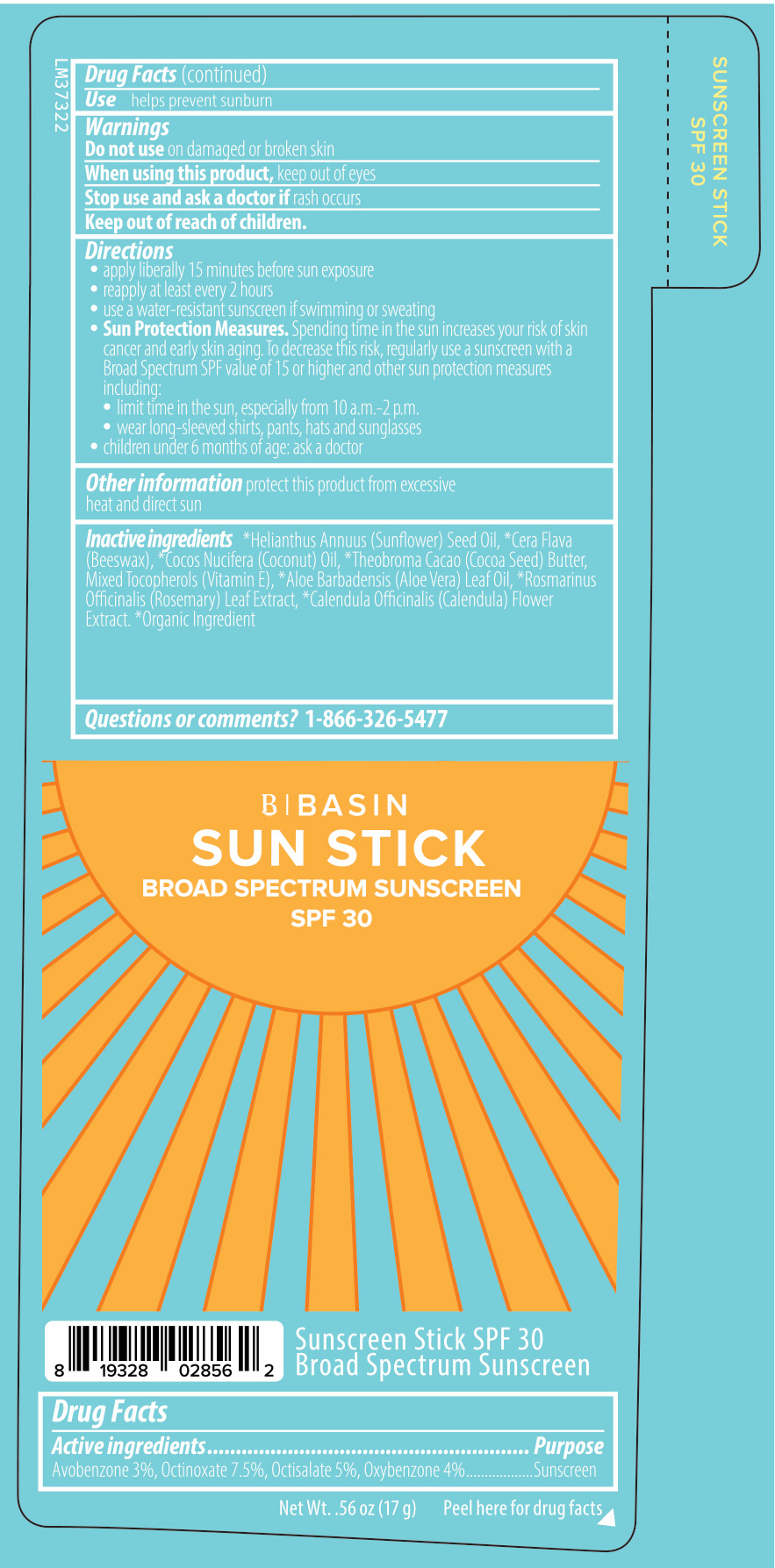 DRUG LABEL: Basin Sun Stick
NDC: 84603-166 | Form: STICK
Manufacturer: Retail Concepts of Minnesota, Inc.
Category: otc | Type: HUMAN OTC DRUG LABEL
Date: 20250910

ACTIVE INGREDIENTS: OCTINOXATE 7.5 g/100 g; OXYBENZONE 4 g/100 g; AVOBENZONE 3 g/100 g; OCTISALATE 5 g/100 g
INACTIVE INGREDIENTS: ROSEMARY OIL; ALOE VERA LEAF; CALENDULA OFFICINALIS FLOWER; YELLOW WAX; SUNFLOWER OIL; COCOA BUTTER; TOCOPHEROL; COCONUT OIL

Basin Sun Stick - 166S SPF 30 Face Stick 0.56 oz tube

Drug Facts

Active ingredients

Avobenzone 3%, Octinoxate 7.5%, Octisalate 5%, Oxybenzone 4%

Purpose

Sunscreen

INDICATIONS AND USAGE

Usehelps prevent sunburn

Warnings

Do not use on damaged or broken skin

When using this product, keep out of eyes

Stop use and ask a doctor if rash occurs

Keep out of reach of children.

Directions

- apply liberally 15 minutes before sun exposure
- reapply at least every 2 hours
- use a water-resistant sunscreen if swimming or sweating
- Sun Protection Measures. Spending time in the sun increases your risk of skin cancer and early skin aging. To decrease this risk, regularly use a sunscreen with a Broad Spectrum SPF value of 15 or higher and other sun protection measures including:
- limit time in the sun, especially from 10 a.m. - 2 p.m.
- wear long-sleeved shirts, pants, hats and sunglasses
- children under 6 months of age: ask a doctor

STORAGE AND HANDLING

Other informationprotect this product from excessive heat and direct sun

INACTIVE INGREDIENT

Inactive ingredients*Helianthus Annuus (Sunflower) Seed Oil, *Cera Flava (Beeswax), *Cocos Nucifera (Coconut Oil), *Theobroma Cacao (Cocoa Seed) Butter, Mixed Tocopherols (Vitamin E), *Aloe Barbadensis (Aloe Vera) Leaf Oil, *Rosmarinus Officinalis (Rosemary) Leaf Extract, *Calendula Officinalis (Calendula) Flower Extract. *Organic Ingredient

Questions or comments?1-866-326-5477

B | BASIN

SUN STICK

BROAD SPECTRUM SUNSCREEN

SPF 30

Sunscreen Stick SPF 30

Broad Spectrum Sunscreen

Net Wt. .56 oz (17 g) Peel Here for drug facts

SUNSCREEN STICK

SPF 30